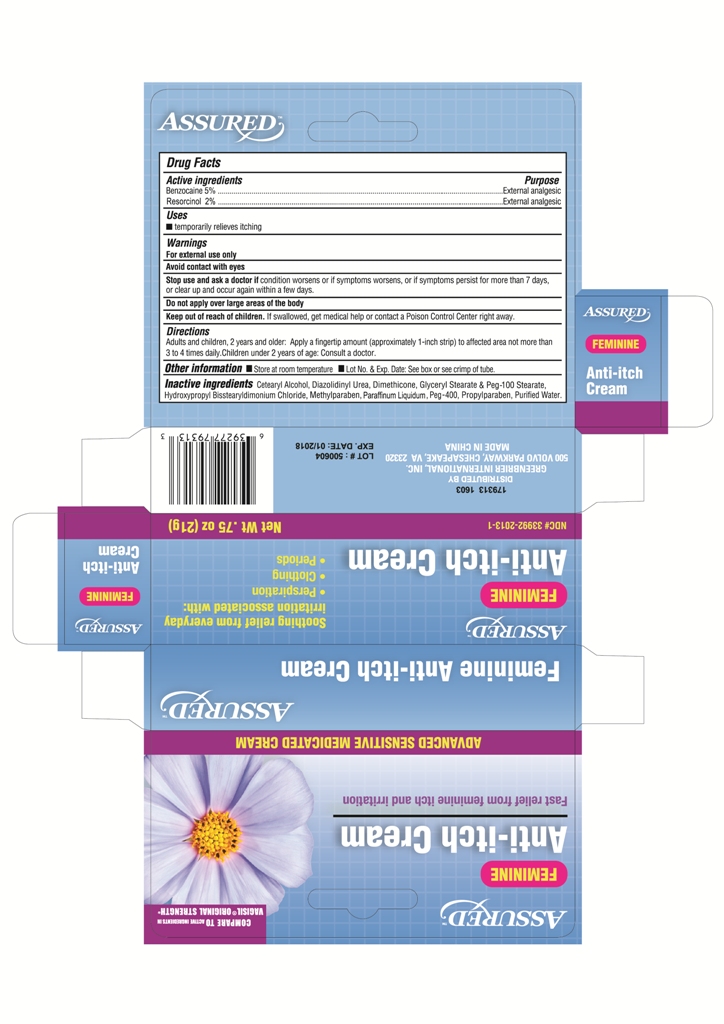 DRUG LABEL: Assured
NDC: 33992-2014 | Form: CREAM
Manufacturer: Greenbrier International
Category: otc | Type: HUMAN OTC DRUG LABEL
Date: 20170404

ACTIVE INGREDIENTS: BENZOCAINE 5 g/100 g; RESORCINOL 2 g/100 g
INACTIVE INGREDIENTS: WATER; POLYETHYLENE GLYCOL 400; CETOSTEARYL ALCOHOL; MINERAL OIL; HYDROXYPROPYL BISSTEARYLDIMONIUM CHLORIDE; DIMETHICONE; GLYCERYL MONOSTEARATE; PEG-100 STEARATE; DIAZOLIDINYL UREA; METHYLPARABEN; PROPYLPARABEN

Drug Facts

Active ingredients

Benzocaine 5%

Resorcinol 2%

Purpose

External analgesic

External analgesic

Uses

■ temporarily relieves itching

Warnings

For external use only

Avoid contact with eyes

Stop use and ask a doctor if

condition worsens or if symptoms persist for more than 7 days or clear up and occur again within a few days

Do not apply over large areas of the body

Keep out of reach of children

If swallowed get medical help or contact a Poison Control Center right away

Directions

Adults and children 2 years of age and older: Apply a fingertip amount (approximately 1-inch strip) to affected area not more than 3 to 4 times daily. Children under 2 years of age: Consult a doctor

Other information

■ Store at room temperature ■ Lot. No. & Exp. Date: See box or see crimp of tube

Inactive ingredients

Cetearyl Alcohol, Diaziolidinyl Urea, Dimethicone, Glyceryl Stearate & Peg 100 Stearate, Hydroxpropyl Bisstearyldimonium Chloride, Methyparaben, Paraffinum Liquidum,Peg 400, Propylparaben, Purified water